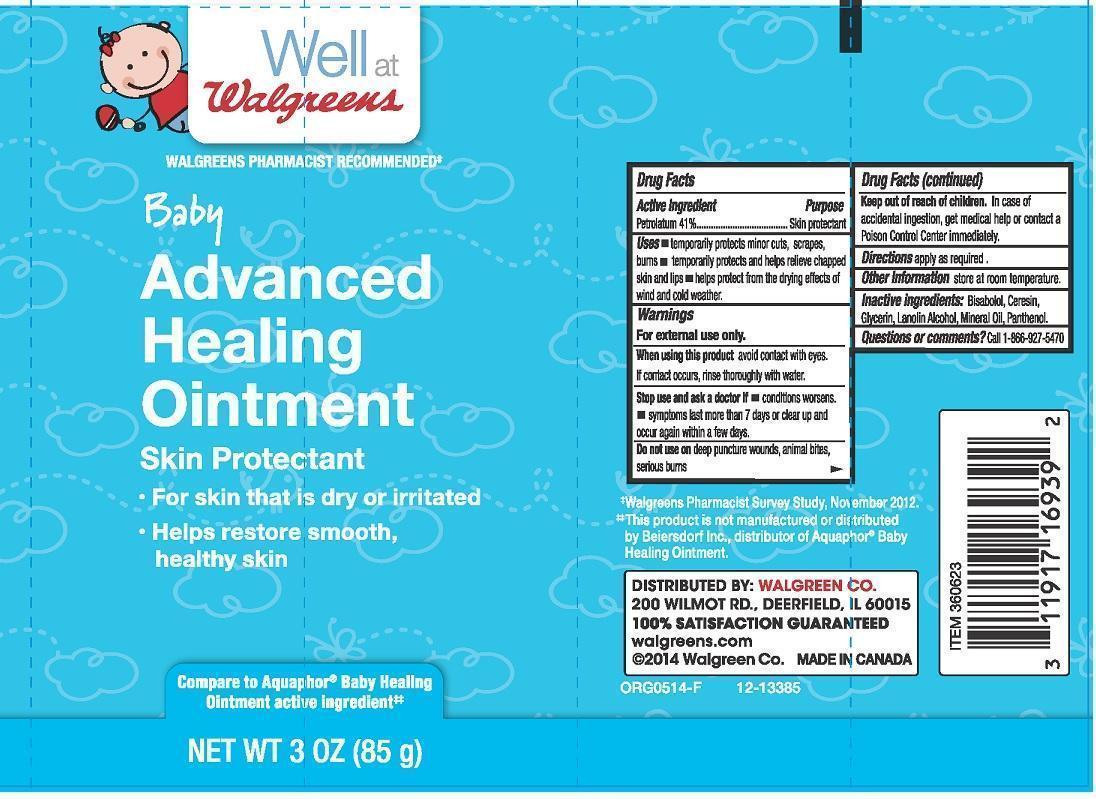 DRUG LABEL: WELL AT WALGREENS
NDC: 0363-3300 | Form: LOTION
Manufacturer: WALGREEN COMPANY
Category: otc | Type: HUMAN OTC DRUG LABEL
Date: 20240618

ACTIVE INGREDIENTS: PETROLATUM 0.41 g/1 g
INACTIVE INGREDIENTS: LANOLIN ALCOHOLS; MINERAL OIL; PANTHENOL; LEVOMENOL; CERESIN; GLYCERIN

DRUG FACTS

ACTIVE INGREDIENT

PETROLATUM 41%

PURPOSE

SKIN PROTECTANT

USES

TEMPORARILY PROTECTS MINOR CUTS, SCRAPES, BURNS. TEMPORARILY PROTECTS AND HELPS RELIEVE CHAPPED SKIN AND LIPS. HELPS PROTECT FROM THE DRYING EFFECTS OF WIND AND COLD WEATHER.

WARNINGS

FOR EXTERNAL USE ONLY

WHEN USING THIS PRODUCT

AVOID CONTACT WITH EYES. IF CONTACT OCCURS, RINSE THOROUGHLY WITH WATER

STOP USE AND ASK A DOCTOR IF

CONDITIONS WORSENS. SYMPTOMS LAST MORE THAN 7 DAYS OR CLEAR UP AND OCCUR AGAIN WITHIN A FEW DAYS

DO NOT USE ON

DEEP PUNCTURE WOUNDS, ANIMAL BITES, SERIOUS BURNS

KEEP OUT OF REACH OF CHILDREN

IN CASE OF ACCIDENTAL INGESTION, GET MEDICAL HELP OR CONTACT A POISON CONTROL CENTER IMMEDIATELY

DIRECTIONS

APPLY AS REQUIRED

OTHER INFORMATION

STORE AT ROOM TEMPERATURE

INACTIVE INGREDIENTS

BISABOLOL, CERESIN, GLYCERIN, LANOLIN ALCOHOL, MINERAL OIL, PANTHENOL

QUESTIONS OR COMMENTS?

CALL 1-866-927-5470